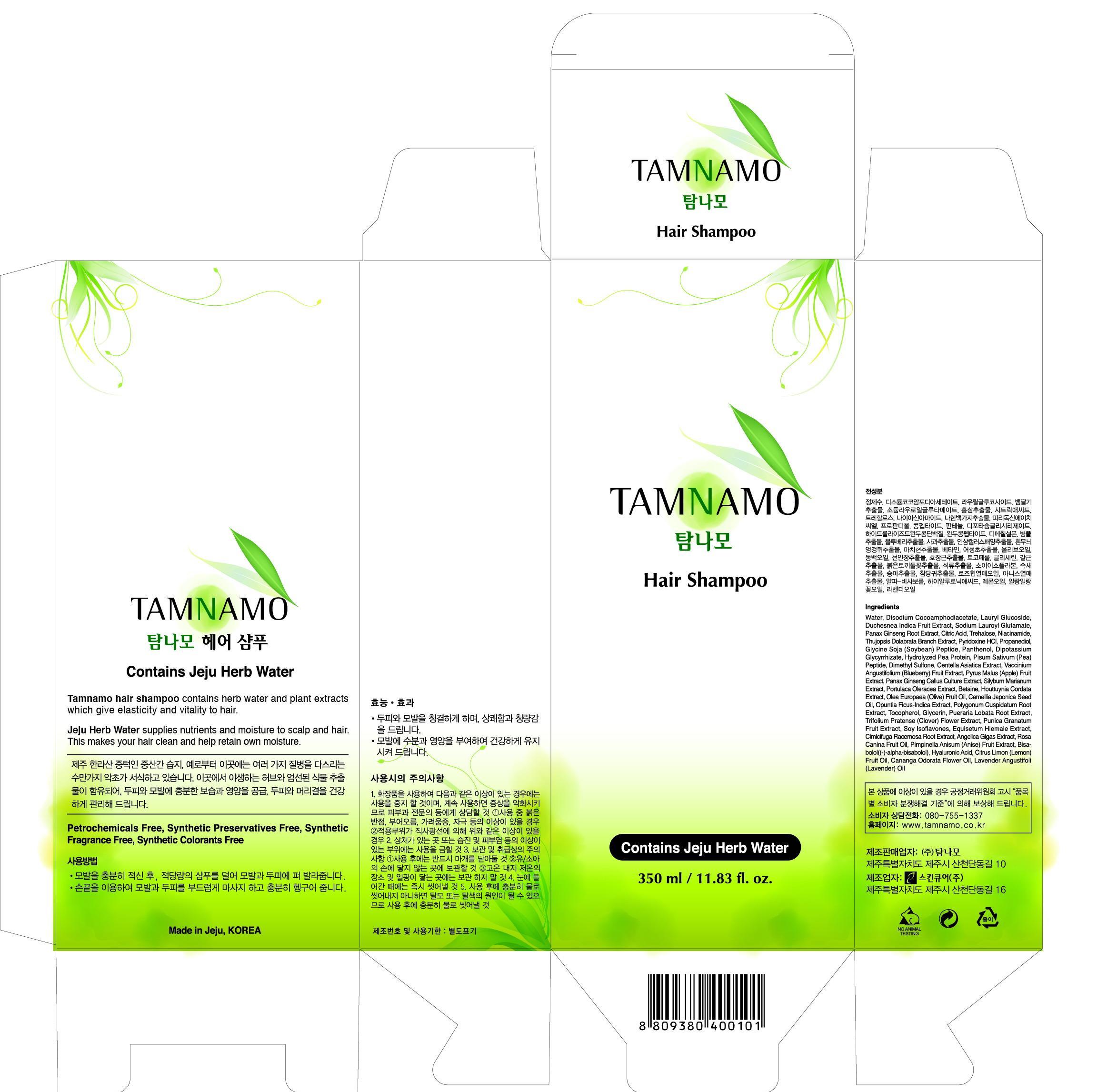 DRUG LABEL: TAMNAMO ESSENTIAL HAIR
NDC: 60344-1001 | Form: SHAMPOO
Manufacturer: Tamnamo Co., Ltd
Category: otc | Type: HUMAN OTC DRUG LABEL
Date: 20130826

ACTIVE INGREDIENTS: GLYCERIN 0.04 g/1 mL
INACTIVE INGREDIENTS: WATER; NIACINAMIDE; CITRIC ACID MONOHYDRATE; PANTHENOL

Drug Facts

ACTIVE INGREDIENT

glycerin

INACTIVE INGREDIENT

Water, Disodium Cocoamphodiacetate, Laurtl Glucoside, Dechesnea Indica Friut Extract, Sodium Lauroyl Glutamate, Panax Ginseng Root Extract, Citric Acid, Trehalose, Niacinamide, Thujopsis Dolabrata Branch Extract, Pyridoxine HCI, Propanediol, Glycine Soja (Soybean) Peptide, Panthenol, Dipotassium Gkycyrrhizate, Hydrolyzed Pea Protein, Pisum Sativum (Pea) Peptide, Dimethyl Sulfone, Centella Asiatica Extract, Vaccinium Augustifolium (Blueberry) Fruit Extract, Pyrus Malus (Apple) Fruit Extract, Panax Ginseng Callus Culture Extract, Silybum Marianum Extract, Portulaca Olercea Extract, Betaince, Houttuyia Cordata Extract, Olea Europaea (Obliv) Fruit Oil, Camellia Japonica Seed Oil, Opintia Ficuz-Indica Extract, Polugonum Cuspidatum Root Trifolium Pratense (Clover) Flower Extract, Pucina Grantaum Fruit Extract, Soy Isoflavones, Equisetum Hiemale Extract, Cimicifuga Ravemosa Root Extract, Angelica Gigas Extrat, Tosa Canina Fruit Oil, Pimpinella Anisum (Anise) Fruit Extrat, Bisabolol ((-)-alpha-bisabolol). Hyaluronic Acis, Citrus Limon (Lemon) Fruit Oil, Canaga Odorata Flower Oil, Lavender Angustifoli (Lavender) Oil

PURPOSE

supplying nutrients and moisture to scalp and hair

keep out of reach of the children

INDICATIONS AND USAGE

Wet hair with worm water
Apply the shampoo work into a rich lather
Massage thoroughly into the hair and scalp
Rinse well and repeat to maximize results

WARNINGS

- Stop using if sensitivities occurs and consult with dermatologist
- sensitivities such as red marks, intumescence, urtication, irritation during use
- Do not store at high and low temperatures and avoid sunlight.

DOSAGE AND ADMINISTRATION

for external use only